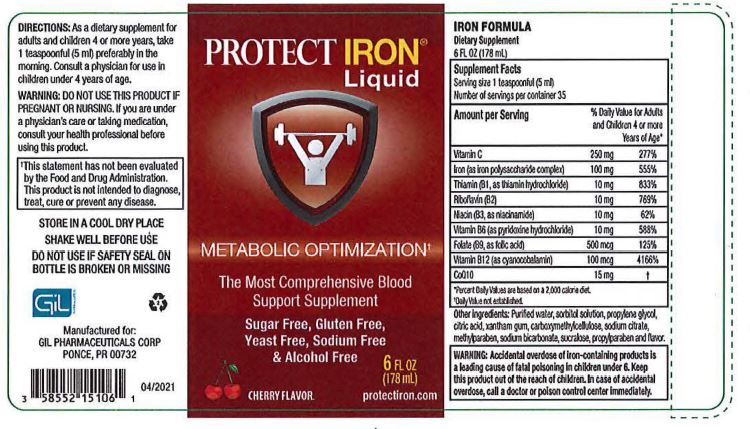 DRUG LABEL: PROTECT IRON Liquid
NDC: 58552-151 | Form: SOLUTION
Manufacturer: GIL Pharmaceutical Corp.
Category: other | Type: DIETARY SUPPLEMENT
Date: 20221105

ACTIVE INGREDIENTS: ASCORBIC ACID 250 mg/1 mL; THIAMINE 10 mg/1 mL; IRON 10 mg/1 mL; RIBOFLAVIN 10 mg/1 mL; NIACIN 10 mg/1 mL; PYRIDOXINE 10 mg/1 mL; FOLIC ACID 500 mg/1 mL; CYANOCOBALAMIN 100 mg/1 mL; UBIDECARENONE 15 mg/1 mL
INACTIVE INGREDIENTS: WATER; SORBITOL SOLUTION; PROPYLENE GLYCOL; CITRIC ACID MONOHYDRATE; XANTHAN GUM; CARBOXYMETHYLCELLULOSE; SODIUM CITRATE; METHYLPARABEN; SODIUM BICARBONATE; SUCRALOSE; PROPYLPARABEN

PROTECT IRON Liquid
METABOLIC OPTIMIZATION
The Most Comprehensive Blood Support Supplement
Sugar Free, Gluten Free, Yeast Free & Alcohol Free

STATEMENT OF IDENTITY

IRON FORMULA

Dietary Supplement

6FL OZ (178 mL)

Supplement Facts

Serving size 1 teaspoonful (5ml)

Number of servings per container 35

Amount Per Serving | %Daily value for Adults and Children 4 or more Years of Age*
Vitamin C | 250mg | 277%
Iron (as iron polysaccharide complex) | 100mg | 555%
Thiamine (B1, as Thiamine hydrochloride) | 10mg | 833%
Riboflavin (B2) | 10mg | 769%
Niacin (B3, as niacinmide) | 10mg | 62%
Vitamin B6 (as pyridoxine hydrochloride) | 10mg | 588%
Folate (B9, as folic acid) | 500 mg | 125%
Vitamin B12 (as cyanocobalamin) | 100 mg | 4166%
CoQ10 | 15 mg | †
*Percent Daily Values are based on a 2000 Calorie diet.
*Daily Values not established.

Other Ingredients: Purified water, sorbitol solution, propylene glycol, citric acid, xanthium gum, carboxymethylcellulose, sodium citrate, methylparaben, sodium bicarbonate, sucralose, propylparaben and flavour.

WARNINGS

WARNING: Accidental overdose of iron-containing product is a leading cause of fatal poisoning in children under 6. Keep this product out of the reach of children. In case of accidental overdose, call a doctor or poison control center immediately.

DOSAGE AND ADMINISTRATION

DIRECTIONS: As a dietary supplement for adults and children 4 or more years, take1 teaspoonful (5ml) preferably in the morning. Consult a physician for use In Children under 4 years of age.

PRECAUTIONS

WARNING: DO NOT USE THIS PRODUCT IF PREGANT OR NURSING. If you are under a physician's care or taking medication, consult your health professional before using this product.

†This statement has not been evaluated by the Food and Drug Administration.This product is not Intended to diagnose, treat, cure or prevent any disease.

SAFE HANDLING WARNING

STORE IN A COOL DRY PLACE

SHAKE WELL BEFORE USE

DO NOT USE IF SAFETY SEAL ON BOTTLE IS BROKEN OR MISSING

Manufactured for:

GIL PHARMACEUTICALS CORP

PONCE, PR 00732

04/2021

PACKAGE LABEL. PRINCIPAL DISPLAY PANEL

Protect-iron-6FLOZ-178ml-NDC-58552-151-06-Bottle